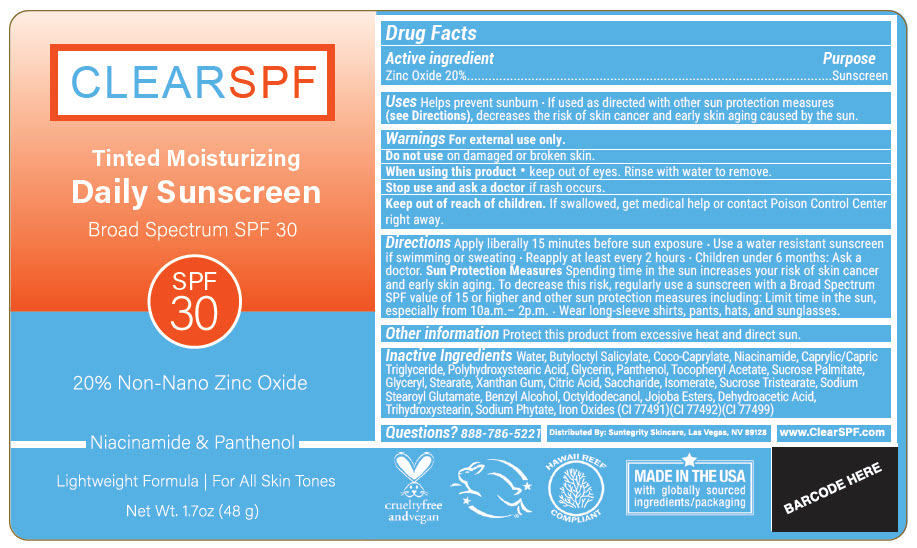 DRUG LABEL: ClearSPF Tinted Sunscreen
NDC: 69949-251 | Form: LOTION
Manufacturer: Synchronicity Spa, Inc. DBA Suntegrity
Category: otc | Type: HUMAN OTC DRUG LABEL
Date: 20241121

ACTIVE INGREDIENTS: ZINC OXIDE 20 g/100 g
INACTIVE INGREDIENTS: WATER; BUTYLOCTYL SALICYLATE; COCO-CAPRYLATE; NIACINAMIDE; MEDIUM-CHAIN TRIGLYCERIDES; POLYHYDROXYSTEARIC ACID (2300 MW); GLYCERIN; PANTHENOL; .ALPHA.-TOCOPHEROL ACETATE; SUCROSE PALMITATE; GLYCERYL MONOSTEARATE; XANTHAN GUM; CITRIC ACID MONOHYDRATE; SACCHARIDE ISOMERATE; SUCROSE TRISTEARATE; SODIUM STEAROYL GLUTAMATE; BENZYL ALCOHOL; OCTYLDODECANOL; JOJOBA OIL; DEHYDROACETIC ACID; TRIHYDROXYSTEARIN; PHYTATE SODIUM; FERRIC OXIDE RED; FERRIC OXIDE YELLOW; FERROSOFERRIC OXIDE

ClearSPF Tinted Sunscreen

Drug Facts

Active ingredient

Zinc Oxide 20%

Purpose

Sunscreen

Uses

Helps prevent sunburn

- If used as directed with other sun protection measures (see Directions), decreases the risk of skin cancer and early skin aging caused by the sun.

Warnings

For external use only.

Do not use on damaged or broken skin.

When using this product

- keep out of eyes. Rinse with water to remove.

Stop use and ask a doctor if rash occurs.

Keep out of reach of children. If swallowed, get medical help or contact Poison Control Center right away.

Directions

Apply liberally 15 minutes before sun exposure

- Use a water resistant sunscreen if swimming or sweating
- Reapply at least every 2 hours
- Children under 6 months: Ask a doctor.

Sun Protection Measures

Spending time in the sun increases your risk of skin cancer and early skin aging. To decrease this risk, regularly use a sunscreen with a Broad Spectrum SPF value of 15 or higher and other sun protection measures including: Limit time in the sun, especially from 10a.m.– 2p.m.

- Wear long-sleeve shirts, pants, hats, and sunglasses.

Other information

Protect this product from excessive heat and direct sun.

Inactive Ingredients

Water, Butyloctyl Salicylate, Coco-Caprylate, Niacinamide, Caprylic/Capric Triglyceride, Polyhydroxystearic Acid, Glycerin, Panthenol, Tocopheryl Acetate, Sucrose Palmitate, Glyceryl, Stearate, Xanthan Gum, Citric Acid, Saccharide, Isomerate, Sucrose Tristearate, Sodium Stearoyl Glutamate, Benzyl Alcohol, Octyldodecanol, Jojoba Esters, Dehydroacetic Acid, Trihydroxystearin, Sodium Phytate, Iron Oxides (CI 77491)(CI 77492)(CI 77499)

Questions?

888-786-5221

Distributed By: Suntegrity Skincare, Las Vegas, NV 89128

PRINCIPAL DISPLAY PANEL - 48 g Bottle Label

CLEARSPF

Tinted Moisturizing
Daily Sunscreen

Broad Spectrum SPF 30

SPF
30

20% Non-Nano Zinc Oxide

Niacinamide & Panthenol

Lightweight Formula | For All Skin Tones

Net Wt. 1.7oz (48 g)